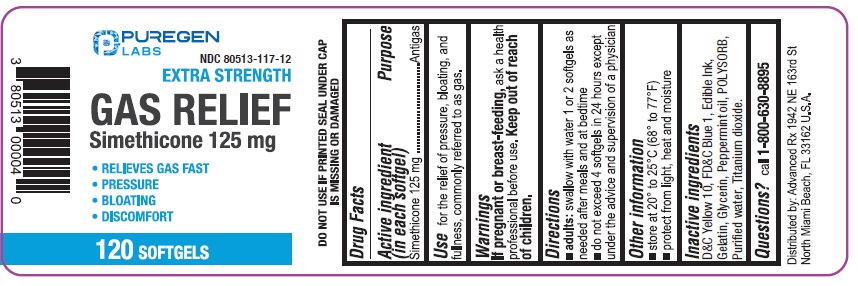 DRUG LABEL: Gas Relief
NDC: 80513-117 | Form: CAPSULE, LIQUID FILLED
Manufacturer: Advanced Rx LLC
Category: otc | Type: HUMAN OTC DRUG LABEL
Date: 20250101

ACTIVE INGREDIENTS: DIMETHICONE 125 mg/1 1
INACTIVE INGREDIENTS: D&C YELLOW NO. 10; FD&C BLUE NO. 1; GELATIN; GLYCERIN; PEPPERMINT OIL; WATER; TITANIUM DIOXIDE

Gas Relief

Active Ingredients (in each softgel)

Simethicone 125 mg

Purpose

Antigas

INDICATIONS AND USAGE

Usefor the relief of pressure, bloating, fullness, commonly referred to as gas.

Warning

If pregnant or breast-feeding,ask a health professional before use.

Directions

- adults: swallow with water 1 or 2 softgels as needed after meals and at bedtime
- do not exceed 4 softgels in 24 hours except under the advice and supervision of a physician

Other Information

- store at 20° to 25°C (68° to 77°F)
- protect from light, heat and moisture
- DO NOT USE IF PRINTED SEAL UNDER CAP IS MISSING OR DAMAGED

INACTIVE INGREDIENT

D&C Yellow 10, FD&C Blue 1, Edible Ink, Gelatin, Glycerin, Peppermint oil, POLYSORB, Purified water, Titanium dioxide.

Questions?

call 1-800-630-8895

Distributed by:

Advanced Rx LLC

1942 NE 163rd St North Miami Beach,

FL 33162 U.S.A.

PACKAGE LABEL

NDC 80513-117-12

Extra Strength

GAS RELIEF

Simethicone 125 mg